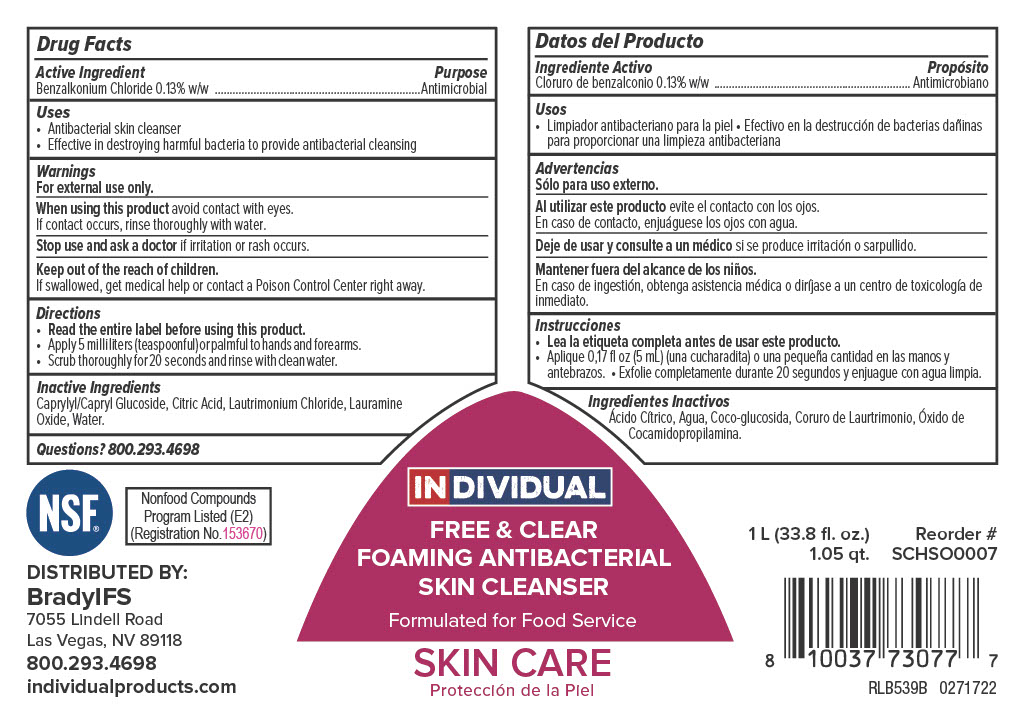 DRUG LABEL: Individual Free and Clear Foaming Antibacterial Skin Cleanser
NDC: 79258-717 | Form: SOAP
Manufacturer: Brady Industries Inc.
Category: otc | Type: HUMAN OTC DRUG LABEL
Date: 20220304

ACTIVE INGREDIENTS: BENZALKONIUM CHLORIDE 1.3 mg/1 mL
INACTIVE INGREDIENTS: ANHYDROUS CITRIC ACID; WATER; LAURAMINE OXIDE; CAPRYLYL GLUCOSIDE; LAURTRIMONIUM CHLORIDE

Individual Free & Clear Foaming Antibacterial Skin Cleanser

Active ingredient

Benzalkonium Chloride 0.13% w/w

Uses

Antibacterial skin cleanser

Effective in destroying harful bacteria to prevent antibacterial cleansing

Warnings

For external use only.

When using this product avoid contact with eyes. If contact occurs, rinse thoroughly with water.

Stop use and ask a doctor if irritation or rash occurs.

Keep out of the reach of children. If swallowed, get medical help or contact a Poison Control Center right away.

Directions

Read entire label before using this product.

Apply 5 milliliters (teaspoonful) or palmful to hands and forearms.

Scrub thoroughly for 20 seconds and rinse with clean water.

Inactive Ingredients

Caprylyl/Capryl Glucoside, Citric Acid, Lautrimonium Chloride, Lauramine Oxide, Water.

Purpose

Antibacterial

Keep out of reach of children

Keep out of the reach of children